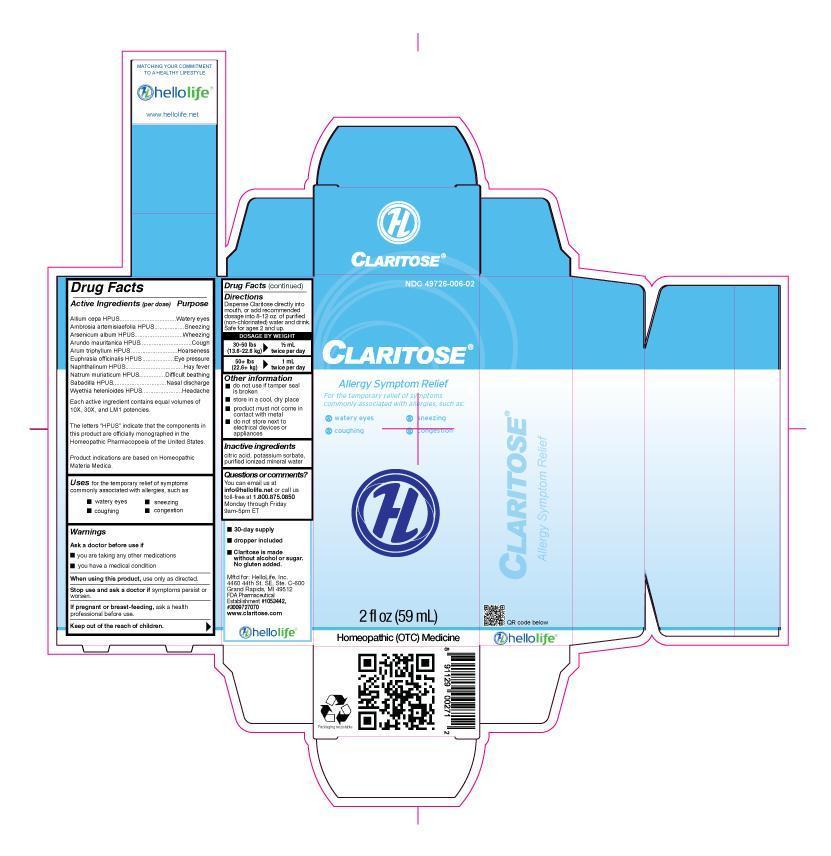 DRUG LABEL: Claritose
NDC: 49726-006 | Form: LIQUID
Manufacturer: Hello Life, Inc.
Category: homeopathic | Type: HUMAN OTC DRUG LABEL
Date: 20181226

ACTIVE INGREDIENTS: ONION 10 [hp_X]/59 mL; AMBROSIA ARTEMISIIFOLIA 10 [hp_X]/59 mL; ARSENIC TRIOXIDE 10 [hp_X]/59 mL; ARUNDO PLINIANA ROOT 10 [hp_X]/59 mL; ARISAEMA TRIPHYLLUM ROOT 10 [hp_X]/59 mL; EUPHRASIA STRICTA 10 [hp_X]/59 mL; NAPHTHALENE 10 [hp_X]/59 mL; SODIUM CHLORIDE 10 [hp_X]/59 mL; SCHOENOCAULON OFFICINALE SEED 10 [hp_X]/59 mL; WYETHIA HELENIOIDES ROOT 10 [hp_X]/59 mL
INACTIVE INGREDIENTS: POTASSIUM SORBATE; WATER; CITRIC ACID MONOHYDRATE

Drug Facts

Active Ingredients (per dose)

Allium cepa HPUS
Ambrosia artemisiaefolia HPUS
Arsenicum album HPUS
Arundo mauritanica HPUS
Arum triphyllum HPUS
Euphrasia officinalis HPUS
Naphthalinum HPUS
Natrum muriaticum HPUS
Sabadilla HPUS
Wyethia helenioides HPUS

Each active ingredient contains equal volumes of 10X, 30X, and LM1 potencies. The letters “HPUS” indicate that the components in this product are officially monographed in the Homeopathic Pharmacopoeia of the United States. Product indications are based on Homeopathic Materia Medica.

Purpose

Allium cepa HPUS……………………………………………….Watery eyes
Ambrosia artemisiaefolia HPUS……………………………… Sneezing
Arsenicum album HPUS……………………………………….Wheezing
Arundo mauritanica HPUS……………………………………Cough
Arum triphyllum HPUS………………………………………...Hoarseness
Euphrasia officinalis HPUS..…………………………………Eye pressure
Naphthalinum HPUS…………………………………………..Hay Fever
Natrum muriaticum HPUS…………………………………….Difficult breathing
Sabadilla HPUS…………………………………………………Nasal discharge
Wyethia helenioides HPUS……………………………………Headache

Uses

for the temporary relief of symptoms commonly associated with allergies, such as:
• watery eyes
• coughing
• sneezing
• congestion

Indications based on Homeopathic Materia Medic for self-limiting conditions.

Warnings

Ask a doctor before use if

- you are taking any other medications
- you have a medical condition

When using this product, use only as directed.

Stop use and ask a doctor if symptoms persist or worsen.

PREGNANCY OR BREAST FEEDING

If pregnant or breast-feeding, ask a health professional before use.

Keep out of the reach of children.

Directions

Dispense Claritose directly into mouth, or add recommended dosage into 8-12 oz. of purified (non-chlorinated) water and drink. Safe for ages 2 and up.

DOSAGE BY WEIGHT

30-50 lbs 1/2 mL
(13.6-22.6 kg) twice per day
50+ lbs 1 mL
(22.6+ kg) twice per day

Other information

• do not use if tamper seal is broken
• store in a cool, dry place
• product must not come in contact with metal
• do not store next to electrical devices or appliances

Inactive ingredients

citric acid, potassium sorbate, purified ionized mineral water.

Questions or comments?

You can email us at info@hellolife.net or call us toll-free at
1.800.875.0850. Monday through Friday, 9am-5pm ET

DESCRIPTION

- 30-day supply
- dropper included
- Claritose is made without alcohol or sugar. No gluten added.

Mftd for: HelloLife, Inc.
4460 44th St. SE, Ste. C-600
Grand Rapids, MI 49512
FDA Pharmaceutical Establishment
#1053442, #3009727070
www.claritose.com

Principal Display Panel

NDC 49726-006-02

CLARITOSE®

Allergy Symptom Relief

For the temporary relief of symptoms commonly associated with allergies, such as:

- watery eyes
- coughing
- sneezing
- congestion

2 fl oz (59 mL)
Homeopathic (OTC) Medicine